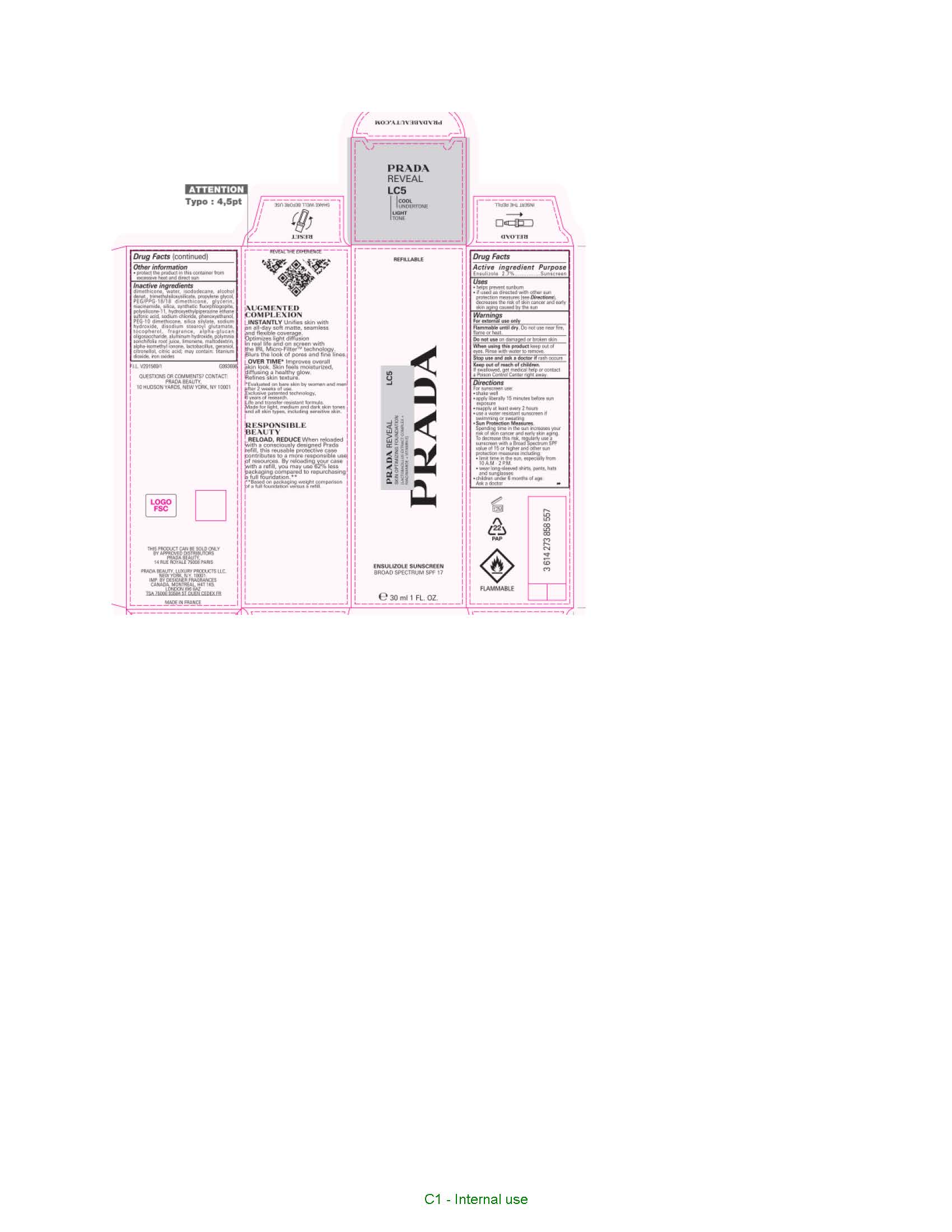 DRUG LABEL: Prada Reveal Skin Optimizing Foundation Broad Spectrum SPF 17 Sunscreen
NDC: 51150-380 | Form: LIQUID
Manufacturer: SICOS ET CIE
Category: otc | Type: HUMAN OTC DRUG LABEL
Date: 20250709

ACTIVE INGREDIENTS: ENSULIZOLE 27 mg/1 mL
INACTIVE INGREDIENTS: DIMETHICONE; WATER; ISODODECANE; ALCOHOL; TRIMETHYLSILOXYSILICATE (M/Q 0.6-0.8); PROPYLENE GLYCOL; PEG/PPG-18/18 DIMETHICONE; GLYCERIN; NIACINAMIDE; SILICON DIOXIDE; DIMETHICONE/VINYL DIMETHICONE CROSSPOLYMER (SOFT PARTICLE); HYDROXYETHYLPIPERAZINE ETHANE SULFONIC ACID; SODIUM CHLORIDE; PHENOXYETHANOL; PEG-10 DIMETHICONE (600 CST); SODIUM HYDROXIDE; DISODIUM STEAROYL GLUTAMATE; TOCOPHEROL; .ALPHA.-GLUCAN OLIGOSACCHARIDE; ALUMINUM HYDROXIDE; LIMONENE, (+)-; MALTODEXTRIN; ISOMETHYL-.ALPHA.-IONONE; LACTOBACILLUS ACIDOPHILUS BCMC 12130; GERANIOL; CITRONELLOL ACETATE, (S)-; CITRIC ACID MONOHYDRATE; TITANIUM DIOXIDE; FERRIC OXIDE RED

Drug Facts

Active ingredient

Ensulizole 2.7%

Purpose

Sunscreen

Uses

- helps prevent sunburn
- if used as directed with other sun protection measures (see Directions), decreases the risk of skin cancer and early skin aging caused by the sun

Warnings

For external use only

Flammable until dry.

Do not use near fire, flame or heat.

Do not use

on damaged or broken skin

When using this product

keep out of eyes. Rinse with water to remove.

Stop use and ask a doctor if

rash occurs

Keep out of reach of children.

If swallowed, get medical help or contact a Poison Control Center right away.

Directions

For sunscreen use:

● shake well before use

● apply liberally 15 minutes before sun exposure

● reapply at least every 2 hours

● use a water resistant sunscreen if swimming or sweating

● Sun Protection Measures. Spending time in the sun increases your risk of skin cancer and early skin aging. To decrease this risk, regularly use a sunscreen with a Broad Spectrum SPF value of 15 or higher and other sun protection measures including:

● limit time in the sun, especially from 10 a.m. – 2 p.m.

● wear long-sleeved shirts, pants, hats, and sunglasses

● children under 6 months of age: Ask a doctor

Other information

protect the product in this container from excessive heat and direct sun

Inactive ingredients

dimethicone, water, isododecane, alcohol denat., trimethylsiloxysilicate, propylene glycol, PEG/PPG-18/18 dimethicone, glycerin, niacinamide, silica, synthetic fluorphlogopite, polysilicone-11, hydroxyethylpiperazine ethane sulfonic acid, sodium chloride, phenoxyethanol, PEG-10 dimethicone, silica silylate, sodium hydroxide, disodium stearoyl glutamate, tocopherol, fragrance, alpha-glucan oligosaccharide, aluminum hydroxide, polymnia sonchifolia root juice, limonene, maltodextrin, alpha-isomethyl ionone, lactobacillus, geraniol, citronellol, citric acid; may contain: titanium dioxide, iron oxides